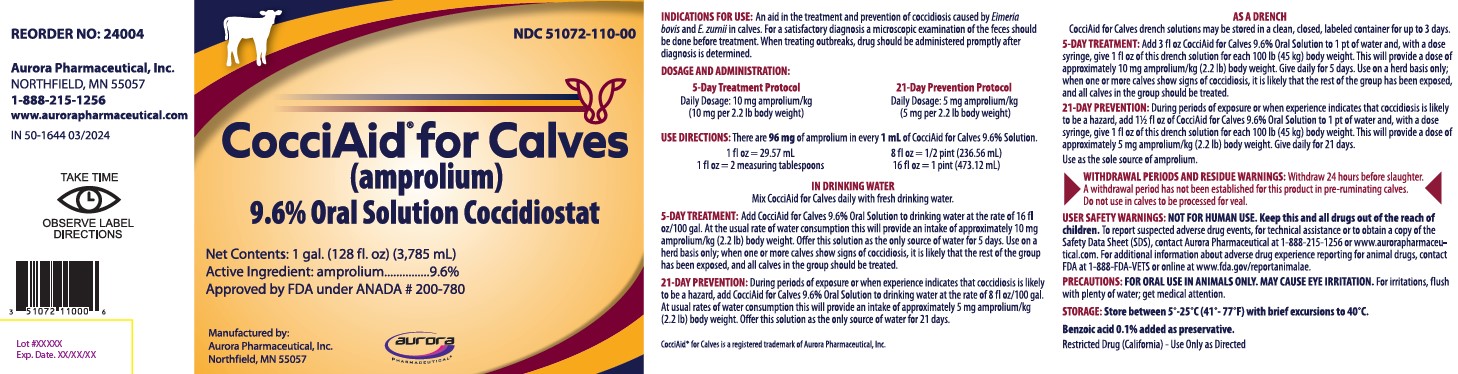 DRUG LABEL: CocciAid for Calves
NDC: 51072-110 | Form: SOLUTION
Manufacturer: Aurora Pharmaceutical, Inc
Category: animal | Type: OTC ANIMAL DRUG LABEL
Date: 20241025

ACTIVE INGREDIENTS: AMPROLIUM 96 mg/1 mL

CocciAid® for Calves

(amprolium)

9.6% Oral Solution Coccidiostat

VETERINARY INDICATIONS

INDICATIONS FOR USE: An aid in the treatment and prevention of coccidiosis caused by Eimeria bovis and E. zurnii in calves. For a satisfactory diagnosis a microscopic examination of the feces should be done before treatment. When treating outbreaks, drug should be administered promptly after diagnosis is determined.

DOSAGE AND ADMINISTRATION:

5-Day Treatment Protocol 21-Day Prevention Protocol
Daily Dosage: 10 mg amprolium/kg Daily Dosage: 5 mg amprolium/kg
(10 mg per 2.2 lb body weight) (5 mg per 2.2 lb body weight)

USE DIRECTIONS: There are 96 mg of amprolium in every 1 mL of CocciAid for Calves 9.6% Solution.

1 fl oz = 29.57 mL 8 fl oz = 1/2 pint (236.56 mL)
1 fl oz = 2 measuring tablespoons 16 fl oz = 1 pint (473.12 mL)

IN DRINKING WATER

Mix CocciAid for Calves daily with fresh drinking water.

5-DAY TREATMENT: Add CocciAid for Calves 9.6% Oral Solution to drinking water at the rate of 16 fl oz/100 gal. At the usual rate of water consumption this will provide an intake of approximately 10 mg amprolium/kg (2.2 lb) body weight. Offer this solution as the only source of water for 5 days. Use on a herd basis only; when one or more calves show signs of coccidiosis, it is likely that the rest of the group has been exposed, and all calves in the group should be treated.

21-DAY PREVENTION: During periods of exposure or when experience indicates that coccidiosis is likely to be a hazard, add CocciAid for Calves 9.6% Oral Solution to drinking water at the rate of 8 fl oz/100 gal. At usual rates of water consumption this will provide an intake of approximately 5 mg amprolium/kg (2.2 lb) body weight. Offer this solution as the only source of water for 21 days.

CocciAid® for Calves is a registered trademark of Aurora Pharmaceutical, Inc.

AS A DRENCH
CocciAid for Calves drench solutions may be stored in a clean, closed, labeled container for up to 3 days.

5-DAY TREATMENT: Add 3 fl oz CocciAid for Calves 9.6% Oral Solution to 1 pt of water and, with a dose syringe, give 1 fl oz of this drench solution for each 100 lb (45 kg) body weight. This will provide a dose of approximately 10 mg amprolium/kg (2.2 lb) body weight. Give daily for 5 days. Use on a herd basis only; when one or more calves show signs of coccidiosis, it is likely that the rest of the group has been exposed, and all calves in the group should be treated.

21-DAY PREVENTION: During periods of exposure or when experience indicates that coccidiosis is likely to be a hazard, add 1 1/2 fl oz of CocciAid for Calves 9.6% Oral Solution to 1 pt of water and, with a dose syringe, give 1 fl oz of this drench solution for each 100 lb (45 kg) body weight. This will provide a dose of approximately 5 mg amprolium/kg (2.2 lb) body weight. Give daily for 21 days.

Use as the sole source of amprolium.

RESIDUE WARNING

WITHDRAWAL PERIODS AND RESIDUE WARNINGS: Withdraw 24 hours before slaughter. A withdrawal period has not been established for this product in pre-ruminating calves. Do not use in calves to be processed for veal.

WARNINGS

USER SAFETY WARNINGS: NOT FOR HUMAN USE. Keep this and all drugs out of the reach of children.
To report suspected adverse drug events, for technical assistance or to obtain a copy of the Safety Data Sheet (SDS), contact Aurora Pharmaceutical at 1-888-215-1256 or www.aurorapharmaceutical.com. For additional information about adverse drug experience reporting for animal drugs, contact FDA at 1-888-FDA-VETS or online at www.fda.gov/reportanimalae.

PRECAUTIONS

PRECAUTIONS: FOR ORAL USE IN ANIMALS ONLY. MAY CAUSE EYE IRRITATION. For irritations, flush with
plenty of water; get medical attention.

STORAGE AND HANDLING

STORAGE: Store between 5°-25°C (41°- 7°F) with brief excursions to 40°C.

Benzoic acid 0.1% added as preservative.

Restricted Drug (California) - Use Only as Directed

CocciAid® for Calves

(amprolium)

9.6% Oral Solution Coccidiostat

Net Contents: 1 gal. (128 fl. oz) (3,785 ml)

Active Ingredient: amprolium...............9.6%

Approved by FDA under ANADA # 200-780

Distributed by:

Aurora Pharmaceutical, Inc.

Northfield, MN 55057

PACKAGE LABEL

IN 50-1644 rev 03/2024